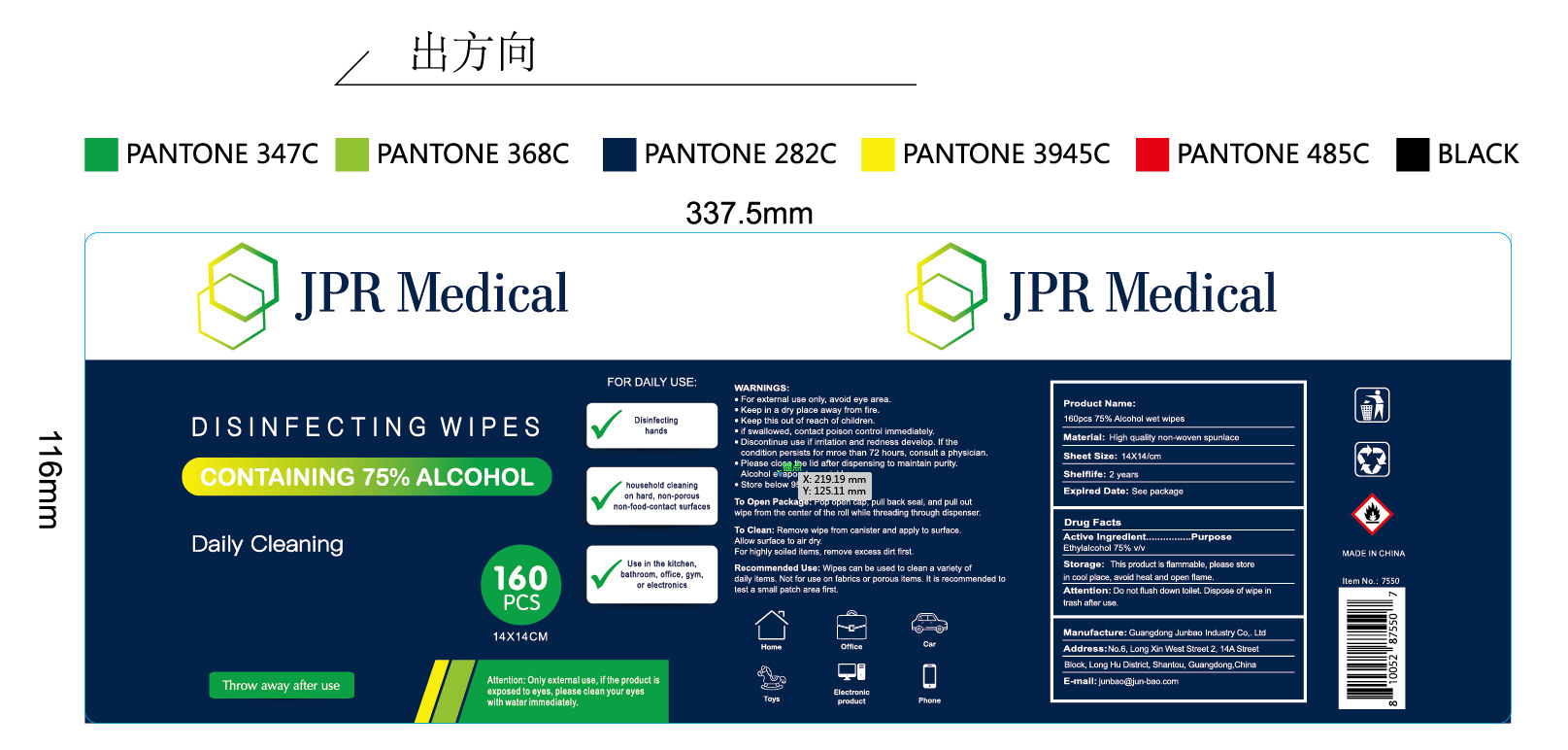 DRUG LABEL: 75% Alcohol Wipes
NDC: 54325-004 | Form: CLOTH
Manufacturer: Guangdong Junbao Industry Co.,Ltd
Category: otc | Type: HUMAN OTC DRUG LABEL
Date: 20220316

ACTIVE INGREDIENTS: ALCOHOL 480 mL/160 1
INACTIVE INGREDIENTS: WATER

DOSAGE AND ADMINISTRATION

Store at room temperature 59°-86°F (15°-30°C)

INACTIVE INGREDIENT

Pure Water

INDICATIONS AND USAGE

Open lid, gently pull back resealable label, remove and use wipe as required. Discard wipe when finished.Reseal package after use to avoid evaporation of alcohol.

ACTIVE INGREDIENT

Ethanol

Keep out of reach of children. If swallowed, get medical help or contact a poison control center immediately.

PURPOSE

Disinfection
Sterilization
No Rinseing

WARNINGS

Flammable- keep away from fire or flame. For external use only.